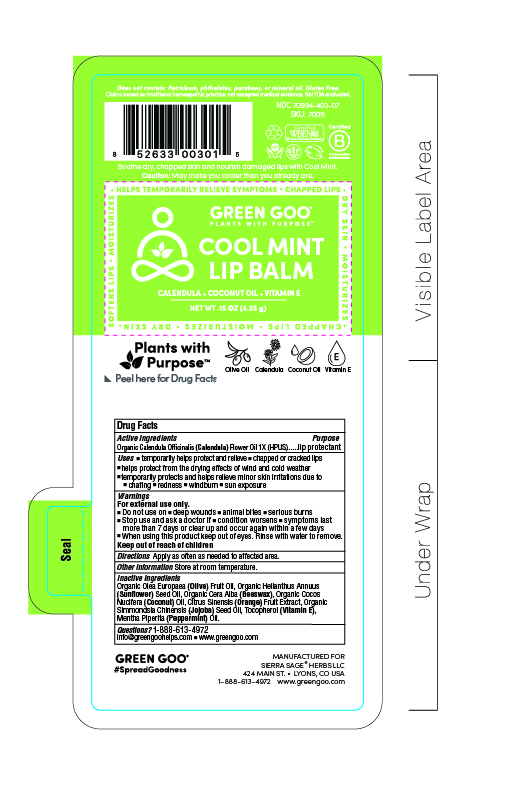 DRUG LABEL: Cool Mint Lip Balm
NDC: 70994-403 | Form: SALVE
Manufacturer: Spry Life LLC
Category: homeopathic | Type: HUMAN OTC DRUG LABEL
Date: 20251215

ACTIVE INGREDIENTS: CALENDULA OFFICINALIS FLOWER 1 [hp_X]/51.7 g
INACTIVE INGREDIENTS: YELLOW WAX; ALPHA-TOCOPHEROL; OLIVE OIL; SUNFLOWER OIL; JOJOBA OIL; COCONUT OIL; MENTHA PIPERITA

Cool Mint Lip Balm

Purpose Section

Skin Protectant

Active Ingredients

Organic Calendula Officinalis (Calendula) Flower Oil 1X (HPUS)

Indications & Usage

■ temporarily helps protect and helps relieve chapped or cracked lips

■ helps protect from the drying effects of wind and cold weather

■ temporarily protects and helps relieve minor skin irritations due to

■ chafing ■ redness ■ windburn ■ sun exposure

Keep out of reach of children section

Keep out of reach of children.

Warnings Section

Warnings

For external use only.

■ Do not use on ■ deep wounds ■ animal bites ■ serious burns

■ Stop use and ask a doctor if conditions worsens symptoms last more than 7 days or clear up and occur again within a few days

■ When using this product keep out of eyes. rinse with water to remove.

Storage

Store at room temperature.

Dosage & Administration Section

Apply as often as needed to affected area.

Inactive Ingredients

Organic Olea Europaea (Olive) Fruit Oil, Organic Helianthus Annuus (Sunflower) Seed Oil, Organic Cera Alba (Beeswax), Organic Cocos Nucifera (Coconut) Oil, Citrus Sinensis (Orange) Fruit Extract, Organic Simmondsia Chinensis (Jojoba) Seed Oil, Tocopherol (Vitamin E), Mentha Piperita (Peppermint) Oil.